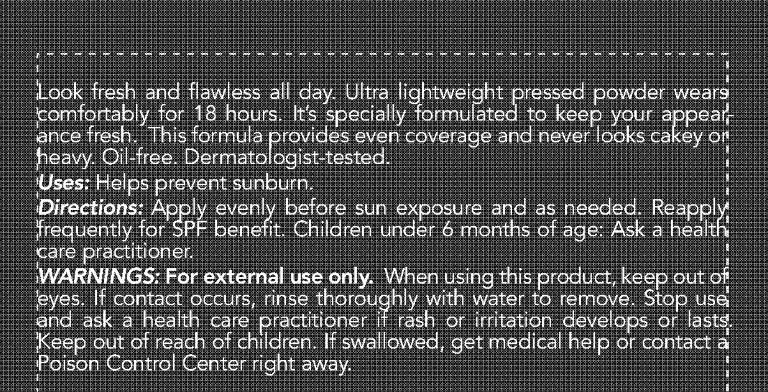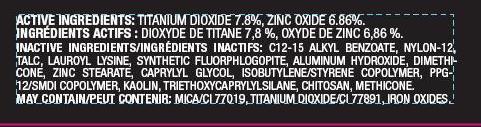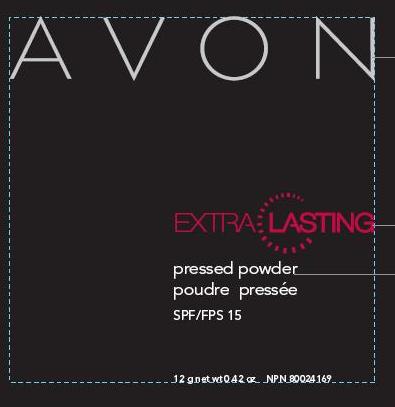 DRUG LABEL: Avon
NDC: 10096-0260 | Form: POWDER
Manufacturer: Avon Products, Inc.
Category: otc | Type: HUMAN OTC DRUG LABEL
Date: 20110422

ACTIVE INGREDIENTS: TITANIUM DIOXIDE	 0.936 g/12 g; ZINC OXIDE	 0.8232 g/12 g

INDICATIONS AND USAGE

Uses: Helps prevent sunburn.

DOSAGE AND ADMINISTRATION

Directions: Apply evenly before sun exposure and as needed. Reapply
frequently for SPF benefit. Children under 6 months of age: Ask a health
care practitioner.

WARNINGS

WARNINGS: For external use only. When using this product, keep out of
eyes. If contact occurs, rinse thoroughly with water to remove. Stop use
and ask a health care practitioner if rash or irritation develops or lasts.
Keep out of reach of children. If swallowed, get medical help or contact a
Poison Control Center right away.

ACTIVE INGREDIENT

ACTIVE INGREDIENTS: TITANIUM DIOXIDE 7.8%, ZINC OXIDE 6.86%.

INACTIVE INGREDIENT

INACTIVE INGREDIENTS/INGRÉDIENTS INACTIFS: C12-15 ALKYL BENZOATE, NYLON-12,
TALC, LAUROYL LYSINE, SYNTHETIC FLUORPHLOGOPITE, ALUMINUM HYDROXIDE, DIMETHICONE,
ZINC STEARATE, CAPRYLYL GLYCOL, ISOBUTYLENE/STYRENE COPOLYMER, PPG-
12/SMDI COPOLYMER, KAOLIN, TRIETHOXYCAPRYLYLSILANE, CHITOSAN, METHICONE.
MAY CONTAIN/PEUT CONTENIR: MICA/CI 77019, TITANIUM DIOXIDE/CI 77891, IRON OXIDES.